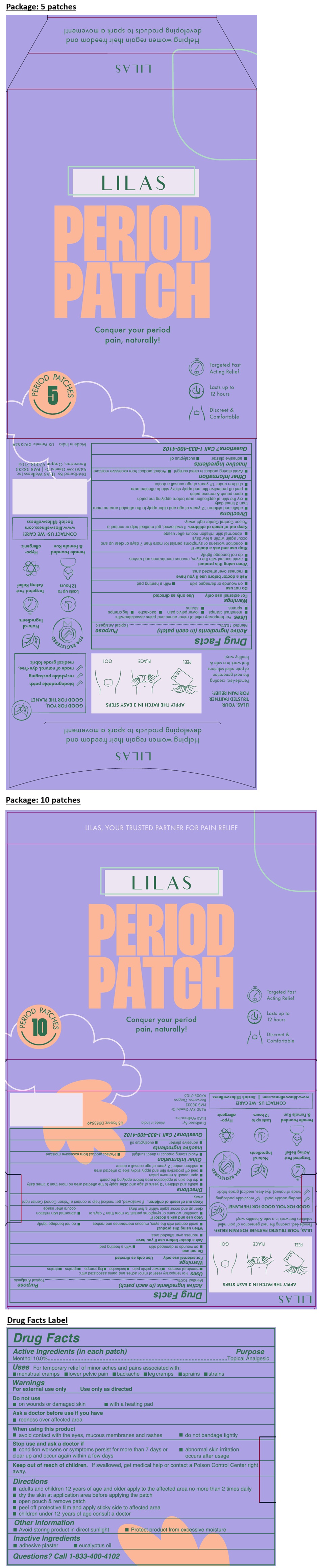 DRUG LABEL: LILAS PERIOD
NDC: 72670-003 | Form: PATCH
Manufacturer: Lilas Wellness, Inc.
Category: otc | Type: HUMAN OTC DRUG LABEL
Date: 20250811

ACTIVE INGREDIENTS: MENTHOL, UNSPECIFIED FORM 200 mg/1 1
INACTIVE INGREDIENTS: EUCALYPTUS OIL

LILAS PERIOD PATCH

Active Ingredients (in each patch)

Menthol 10.0%

Purpose

Topical Analgesic

Uses

For temporary relief of minor aches and pains associated with:
• menstrual cramps • lower pelvic pain • backache • leg cramps • sprains • strains

Warnings

For external use only Use only as directed

Do not use
• on wounds or damaged skin • with a heating pad

Ask a doctor before use if you have
• redness over affected area

When using this product
• avoid contact with the eyes, mucous membranes and rashes • do not bandage tightly

Stop use and ask a doctor if
• condition worsens or symptoms persist for more than 7 days or clear up and occur again within a few days
• abnormal skin irritation occurs after usage

Keep out of reach of children. If swallowed, get medical help or contact a Poison Control Center right away.

Directions

• adults and children 12 years of age and older apply to the affected area no more than 2 times daily
• dry the skin at application area before applying the patch
• open pouch & remove patch
• peel off protective film and apply sticky side to affected area
• children under 12 years of age consult a doctor

Other Information

• Avoid storing product in direct sunlight • Protect product from excessive moisture

Inactive Ingredients

• adhesive plaster • eucalyptus oil

Questions?

Call 1-833-400-4102

Conquer your period pain, naturally!

Targeted Fast Acting Relief

Lasts up to 12 hours

Discreet & Comfortable

APPLY THE PATCH IN 3 EASY STEPS

PEEL PLACE GO!

LILAS, YOUR TRUSTED PARTNER FOR PAIN RELIEF:
Female-led, creating the next generation of pain relief solutions that work in a safe & healthy way!

GOOD FOR YOU, GOOD FOR THE PLANET
✓ biodegradable patch ✓ recyclable packaging
✓ made of natural, dye-free, medical grade fabric

Targeted Fast Acting Relief

Natural Ingredients

FDA REGISTERED

Female Founded & Female Run

Lasts up to 12 hours

Hypo-allergenic

CONTACT US- WE CARE!
www.lilaswellness.com | Social: @lilaswellness

Distributed By:
LILAS Wellness Inc

9450 SW Gemini Dr
PMB 38333
Beaverton, Oregon
97008-7105

Made in India

US Patents: D953549

Helping women regain their freedom and developing products to spark a movement!